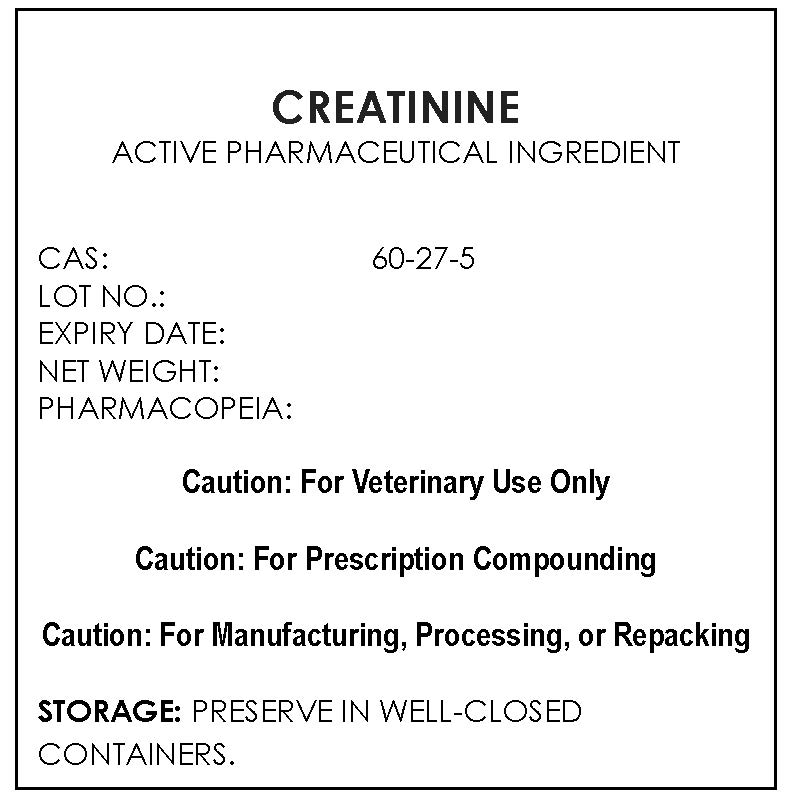 DRUG LABEL: CREATININE
NDC: 43744-062 | Form: POWDER
Manufacturer: CBSCHEM LIMITED
Category: other | Type: BULK INGREDIENT
Date: 20200831

ACTIVE INGREDIENTS: CREATININE 1 g/1 g

CREATININE

PACKAGE LABEL

creatininelabelfile.jpg